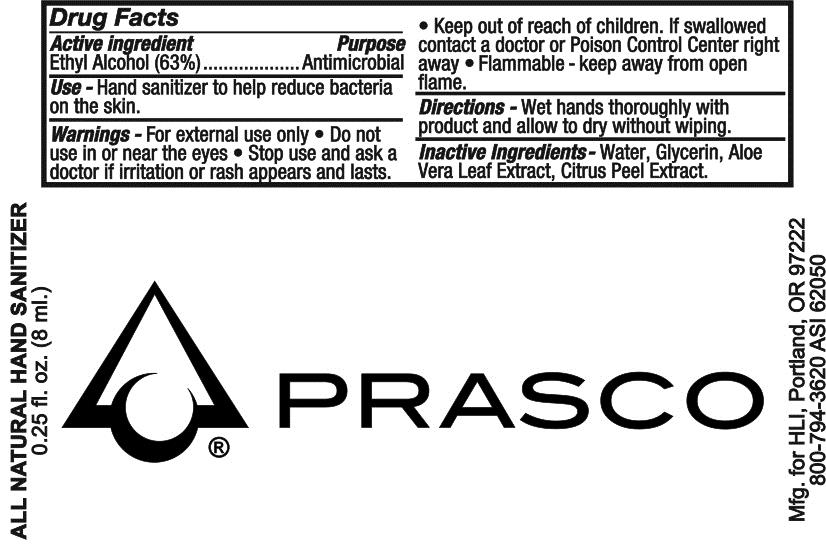 DRUG LABEL: Hand Sanitizer								
NDC: 19392-130 | Form: LIQUID
Manufacturer: Bullet Line, LLC
Category: otc | Type: HUMAN OTC DRUG LABEL
Date: 20211217

ACTIVE INGREDIENTS: ALCOHOL 630 mL/1000 mL
INACTIVE INGREDIENTS: WATER; GLYCERIN; ALOE VERA LEAF; BITTER ORANGE OIL

Drug Facts

ACTIVE INGREDIENT

Ethyl Alcohol (63%)

PURPOSE

Antimicrobial

INDICATIONS AND USAGE

Hand sanitizer to help reduce bacteria on the skin

WARNINGS

For external use only. Do not use in or near the eyes. Stop use and ask a doctor if irritation or rash appears and lasts. Keep out of reach of children. If swallowed contact a doctor or Poison Control Center right away. Flammable-keep away from open flame.

INACTIVE INGREDIENT

Water, Glycerin, Aloe Vera Leaf Extract, Citrus Peel Extract

Keep out of reach of children. If swallowed contact a doctor or Poison Control Center right away.

DOSAGE AND ADMINISTRATION

Wet hands thoroughly with product and allow to dry without wiping.